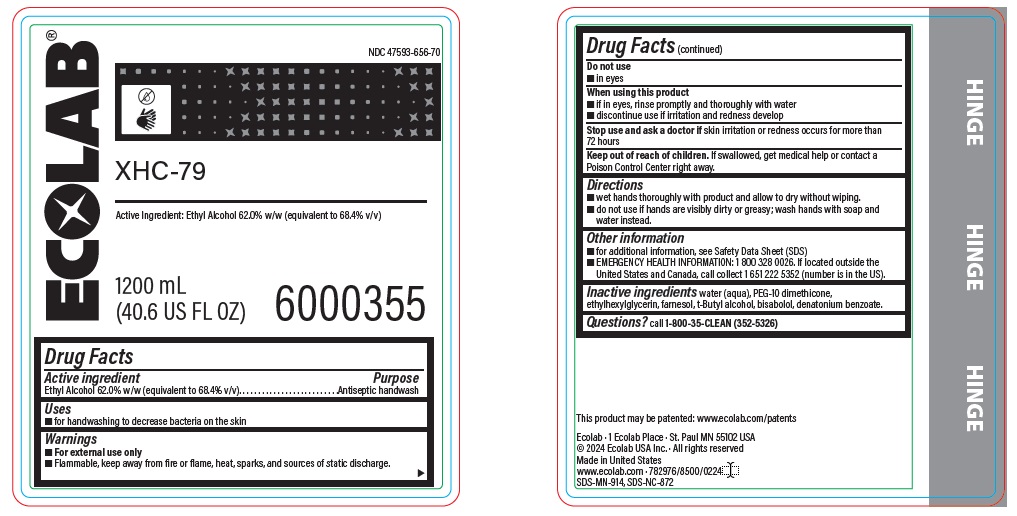 DRUG LABEL: XHC-79
NDC: 47593-656 | Form: SOLUTION
Manufacturer: Ecolab Inc.
Category: otc | Type: HUMAN OTC DRUG LABEL
Date: 20251230

ACTIVE INGREDIENTS: Alcohol 68.4 mL/100 mL
INACTIVE INGREDIENTS: WATER; PEG-10 DIMETHICONE (600 CST); ETHYLHEXYLGLYCERIN; FARNESOL; .ALPHA.-BISABOLOL, (+/-)-; TERT-BUTYL ALCOHOL; DENATONIUM BENZOATE

Drug Facts

Active ingredient

Ethyl Alcohol 62.0% w/w (equivalent to 68.4% v/v)

Purpose

Antiseptic handwash

Uses

- for hand washing to decrease bacteria on the skin

Warnings

- For external use only
- Flammable, keep away from fire or flame, heat sparks and sources of static discharge.

Do not use

- in eyes

When using this product

- if in eyes, rinse promptly and thoroughly with water
- discontinue use if irritation and redness develop

Stop use and ask a doctor if irritation and redness occurs for more than 72 hours.

Keep out of reach of children. If swallowed, get medical help or contact a Poison Control Center right away.

Directions

- wet hands thoroughly with product and allow to dry without wiping.
- do not use if hands are visibly dirty or greasy; wash hands with soap and water instead

Other Information

- for additional information, see Safety Data Sheet (SDS)
- EMERGENCY HEALTH INFORMATION: 1 800 328 0026. If located outside the United States and Canada, call collect 1 651 222 5352 (number is in the US).

Inactive Ingredients

water (aqua), PEG-10 dimethicone, ethylhexylglycerin, farnesol, t-butyl alcohol, bisabolol, denatonium benzoate

Questions? call 1-800-35-CLEAN (352-5326)

Principal display panel and representative label

ECOLAB

47593-656-70

XHC-79

Active Ingredient: Ethyl Alcohol 62.0% w/w (equivalent to 68.4% v/v)

1200 mL

(40.6 US FL OZ) 6000355

Ecolab · 1 Ecolab Place · St. Paul MN 55102 USA

© 2024 Ecolab USA Inc. · All rights reserved

Made in United States

www.ecolab.com · 782976/8500/0224

SDS-MN-914, SDS-NC-872